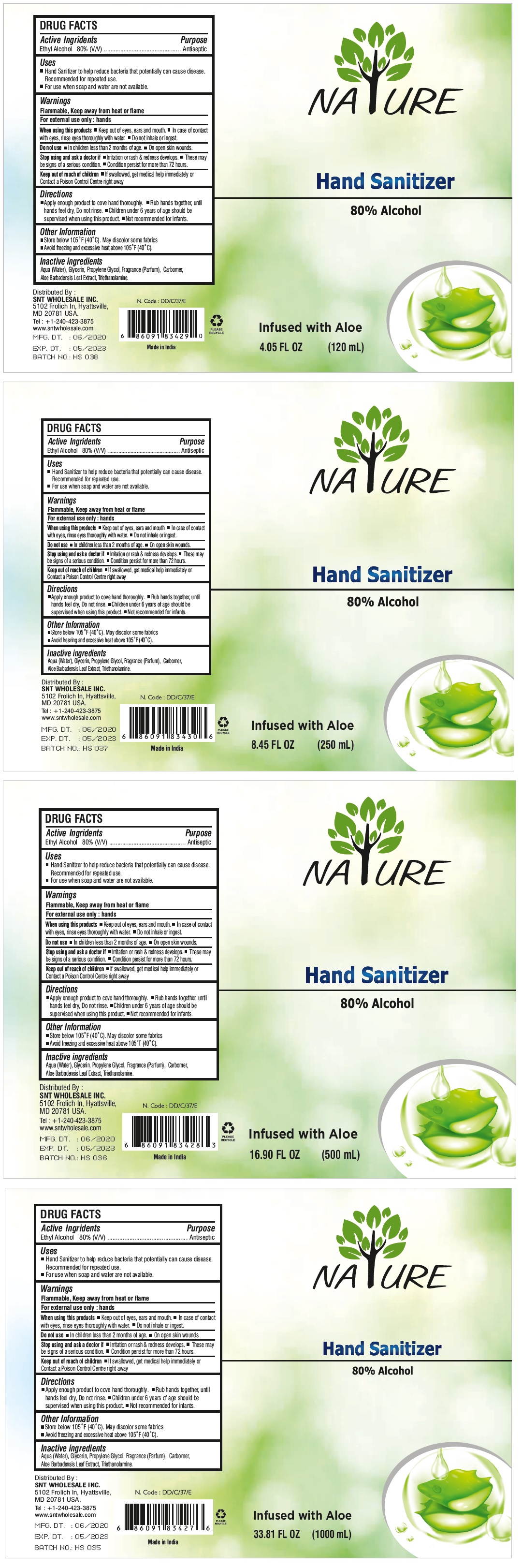 DRUG LABEL: NATURE HAND SANITIZER
NDC: 78914-000 | Form: GEL
Manufacturer: Snt Wholesale, Inc.
Category: otc | Type: HUMAN OTC DRUG LABEL
Date: 20200615

ACTIVE INGREDIENTS: ALCOHOL 80 mL/100 mL
INACTIVE INGREDIENTS: WATER; GLYCERIN; PROPYLENE GLYCOL; CARBOMER HOMOPOLYMER, UNSPECIFIED TYPE; ALOE VERA LEAF; TROLAMINE

NATURE HAND SANITIZER

Active Ingredients

Ethyl Alcohol 80% (v/v)

Purpose

Antiseptic

Uses

- Hand Sanitizer to help reduce bacteria that potentially can cause disease. Recommended for repeated use.
- For use when soap and water are not available.

Warnings

Flammable. Keep away from fire or flame.

For external use only: hands

When using this product ▪ Keep out of eyes, ears and mouth. ▪ In case of contact with eyes, rinse eyes thoroughly with water. ▪ Do not inhale or ingest.

Do not use ▪ In children less than 2 months of age. ▪ On open skin wounds.

Stop use and ask a doctor if ▪ Irritation or rash & redness develops. ▪ These may be signs of a serious condition. ▪ Condition persist for more than 72 hours.

Keep out of reach of children. ▪ If swallowed, get medical help immediately. ▪ Contact a Poison Control Centre right away.

Directions

▪ Apply enough product to cove hand thoroughly. ▪ Rub hands together, until hands feel dry, Do not rinse. ▪ Children under 6 years of age should be supervised when using this product. ▪ Not recommended for infants.

Other information

▪ Store below 105°F (40°C). May discolor some fabrics
▪ Avoid freezing and excessive heat above 105°F (40°C).

Inactive ingredients

Aqua (Water), Glycerin, Propylene Glycol, Fragrance (Parfum), Carbomer, Aloe Barbadensis Leaf Extract, Triethanolamine.

Contains 80% Alcohol

Infused with Aloe

Distributed by:

SNT WHOLESALE INC.

5102 Frolich In, Hyattsville,

MD 20781 USA.

Tel: +1-240-423-3875

www.sntwholesale.com

MFG. DT. : 06/2020

EXP. DT. : 05/2023

BATCH NO.: HS 038

PLEASE RECYCLE

Made In India